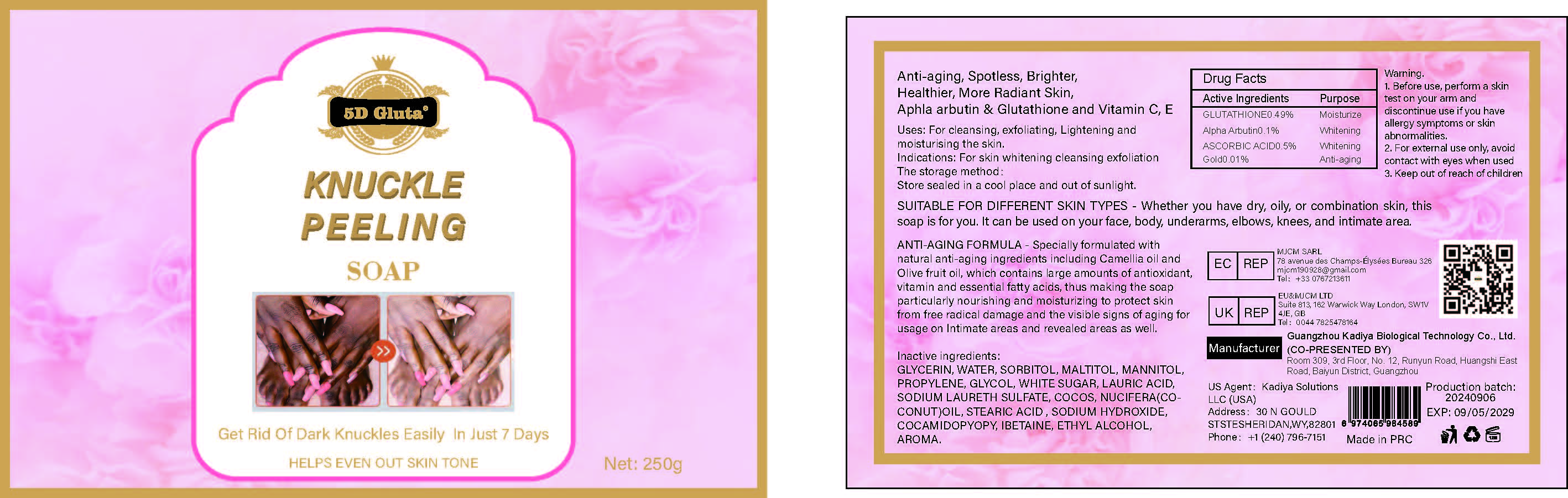 DRUG LABEL: KNUCKLE PEELINGSOAP
NDC: 84423-049 | Form: SOAP
Manufacturer: Guangzhou Kadiya Biotechnology Co., Ltd.
Category: otc | Type: HUMAN OTC DRUG LABEL
Date: 20240928

ACTIVE INGREDIENTS: ASCORBIC ACID 1.25 g/250 g; GLUTATHIONE 1.225 g/250 g; GOLD 0.025 g/250 g; ALPHA-ARBUTIN 0.25 g/250 g
INACTIVE INGREDIENTS: GLYCERIN; SUCROSE; STEARIC ACID; MALTITOL; MANNITOL; PROPYLENE GLYCOL; COCONUT OIL; SODIUM HYDROXIDE; SORBITOL; LAURIC ACID; COCO/OLEAMIDOPROPYL BETAINE; WATER; SHEA BUTTER; ALCOHOL; SODIUM LAURETH SULFATE

Uses：
For cleansing, exfoliating, Lightening and moisturising the skin.

INACTIVE INGREDIENT

GLYCERIN、WATER、SORBITOL、MALTITOL、MANNITOL、PROPYLENE、GLYCOL、WHITE SUGAR、LAURIC ACID、SODIUM LAURETH SULFATE、COCOS、NUCIFERA(COCONUT)OIL、STEARIC ACID 、SODIUM HYDROXIDE、COCAMIDOPYOPY、IBETAINE、ETHYL ALCOHOL、AROMA

Warning.
1.Before use, perform a skin test on your arm and discontinue use if you have allergy symptoms or skin abnormalities.
2、For external use only, avoid contact with eyes when used
3、Keep out of reach of children

DOSAGE AND ADMINISTRATION

SUITABLE FOR DIFFERENT SKIN TYPES- Whether you have dry, oily, or combination skin, this soap is for you. It can be used on your face, body, underarms, elbows, knees, and intimate area.

KEEP OUT OF REACH OF CHILDREN SECTION

Active Ingredients
GLUTATHIONE0.49%
Alpha Arbutin0.1%
ASCORBIC ACID0.5%
Gold0.01%

INDICATIONS AND USAGE

For cleansing, exfoliating, Lightening and moisturising the skin.

PACKAGE LABEL

Active Ingredients
GLUTATHIONE0.49%
Alpha Arbutin0.1%
ASCORBIC ACID0.5%
Gold0.01%
Uses：
For cleansing, exfoliating, Lightening and moisturising the skin.
Indications: For skin whitening cleansing exfoliation
The storage method：
Store sealed in a cool place and out of sunlight
Warning.
1.Before use, perform a skin test on your arm and discontinue use if you have allergy symptoms or skin abnormalities.
2、For external use only, avoid contact with eyes when used
3、Keep out of reach of children
Inactive ingredients：
GLYCERIN、WATER、SORBITOL、MALTITOL、MANNITOL、PROPYLENE、GLYCOL、WHITE SUGAR、LAURIC ACID、SODIUM LAURETH SULFATE、COCOS、NUCIFERA(COCONUT)OIL、STEARIC ACID 、SODIUM HYDROXIDE、COCAMIDOPYOPY、IBETAINE、ETHYL ALCOHOL、AROMA